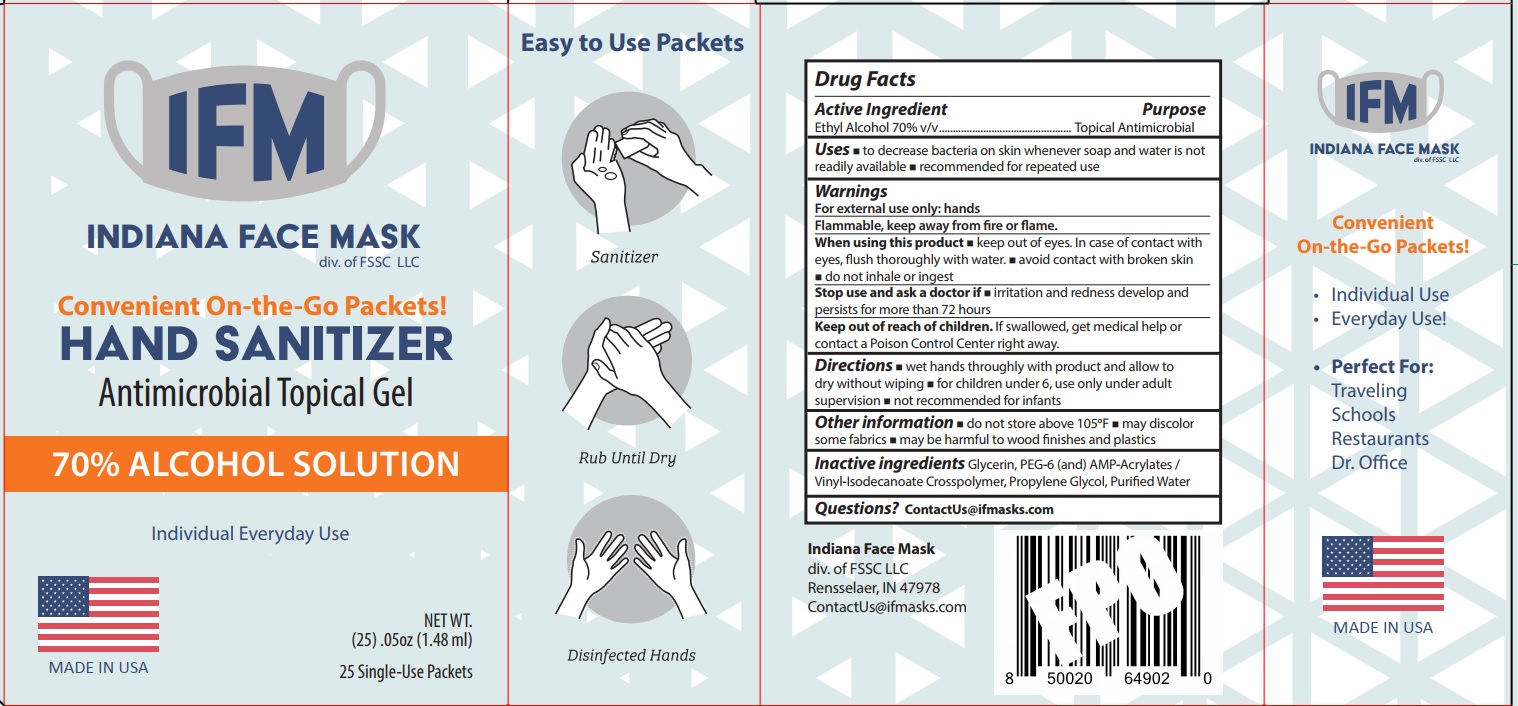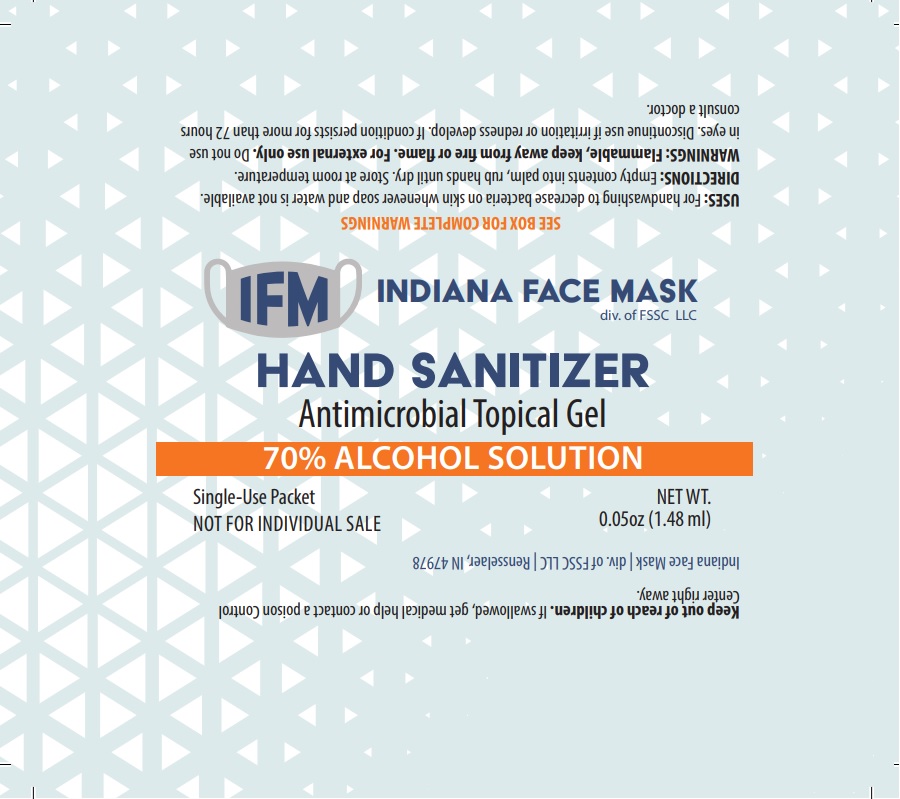 DRUG LABEL: IFM Hand Sanitizer
NDC: 80701-000 | Form: GEL
Manufacturer: FSSC, LLC
Category: otc | Type: HUMAN OTC DRUG LABEL
Date: 20201023

ACTIVE INGREDIENTS: ALCOHOL 0.7 mL/1 mL
INACTIVE INGREDIENTS: GLYCERIN; POLYETHYLENE GLYCOL 300; PROPYLENE GLYCOL; WATER

IFM Hand Sanitizer

Active Ingredient

Ethyl Alcohol 70% v/v

Purpose

Topical Antimicrobial

Uses

- to decrease bacteria on skin whenever soap and water is not readily available
- recommended for repeated use

Warnings

For external use only: hands
Flammable, keep away from fire or flame.

When using this product

- keep out of eyes. In case of contact with eyes, flush thoroughly with water.
- avoid contact with broken skin
- do not inhale or ingest

Stop use and ask a doctor if

- irritation and redness develop and persists for more than 72 hours

Keep out of reach of children.

If swallowed, get medical help or contact a Poison Control Center right away.

Directions

- wet hands throughly with product and allow to dry without wiping
- for children under 6, use only under adult supervision
- not recommended for infants

Other information

- do not store above 105F
- may discolor some fabrics
- may be harmful to wood finishes and plastics

Inactive ingredients

Glycerin, PEG-6 (and) AMP-Acrylates / Vinyl-Isodecanoate Crosspolymer, Propylene Glycol, Purified Water

Questions?

ContactUs@ifmasks.com